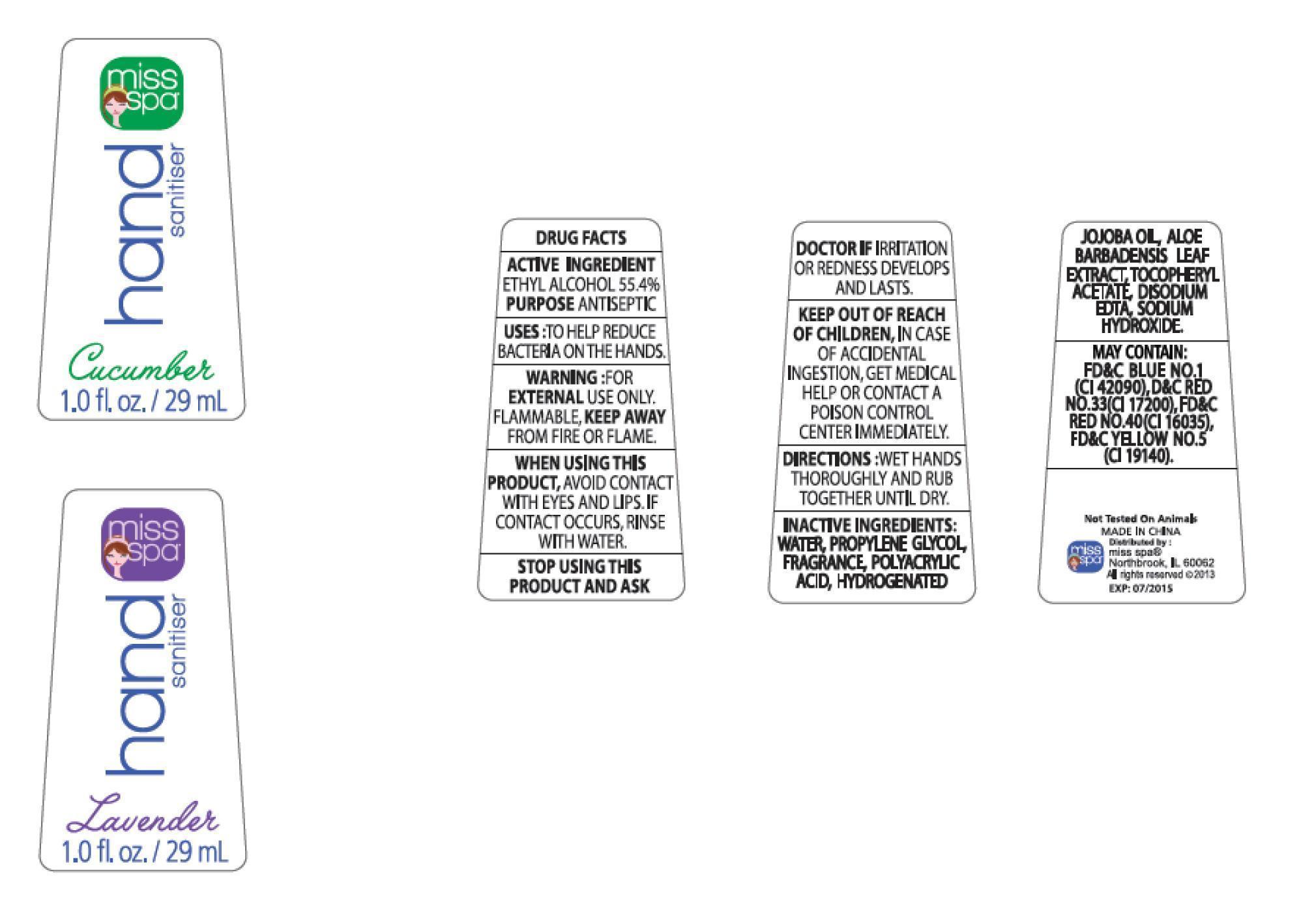 DRUG LABEL: Miss Spa 
NDC: 61238-1125 | Form: GEL
Manufacturer: Oriental Home Sense Co., Ltd.
Category: otc | Type: HUMAN OTC DRUG LABEL
Date: 20131114

ACTIVE INGREDIENTS: ALCOHOL 554 mL/554 mL
INACTIVE INGREDIENTS: WATER; PROPYLENE GLYCOL; POLYACRYLIC ACID (250000 MW); HYDROGENATED JOJOBA OIL/JOJOBA OIL, RANDOMIZED (IODINE VALUE 57-61); ALOE VERA LEAF; TOCOPHERYL RETINOATE; DISODIUM (ETHOXYCARBONYL)PHOSPHONATE; SODIUM HYDRIDE; FD&C YELLOW NO. 5; FD&C BLUE NO. 1; FD&C RED NO. 3

Miss Spa Hand Sanitiser

ACTIVE INGREDIENT: ETHYL ALCOHOL 55.4% PURPOSE ANTISEPTIC

PURPOSE

ANTISEPTIC

INDICATIONS AND USAGE

USES: TO HELP REDUCE BACTERIA ON THE HANDS.

WARNINGS

WARNING: FOR EXTERNAL USE ONLY. FLAMMABLE, KEEP AWAY FROM FIRE OR FLAME.

WHEN USING THIS PRODUCT, AVOID CONTACT WITH EYES AND LIPS. IF CONTACT OCCURS, RINSE WITH WATER.

ASK DOCTOR

STOP USING THIS PRODUCT AND ASK DOCTOR IF IRRITATION OR REDNESS DEVELOPS AND LASTS

KEEP OUT OF REACH OF CHILDREN, IN CASE OF ACCIDENTAL INGESTION, GET MEDICAL HELP OR CONTACT A POISON CONTROL CENTER IMMEDIATELY.

DOSAGE AND ADMINISTRATION

DIRECTIONS: WET HANDS THOROUGHLY AND RUB TOGETHER UNTIL DRY.

INACTIVE INGREDIENT

INACTIVE INGREDIENTS: WATER, PROPYLENE GLYCOL, FRAGRANCE, POLYACRYLIC ACID, HYDROGENATED JOJOBA OIL, ALOE BARBADENSIS LEAF EXTRACT, TOCOPHERYL ACETATE, DISODIUM EDTA, SODIUM HYDROXIDE. MAY CONTAIN: FD&C BLUE NO. 1(CI 42090), D&C RED NO. 33(CI 17200), FD&C RED NO. 40(CI 16035), FD&C YELLOW NO. 5 (CI 19140)